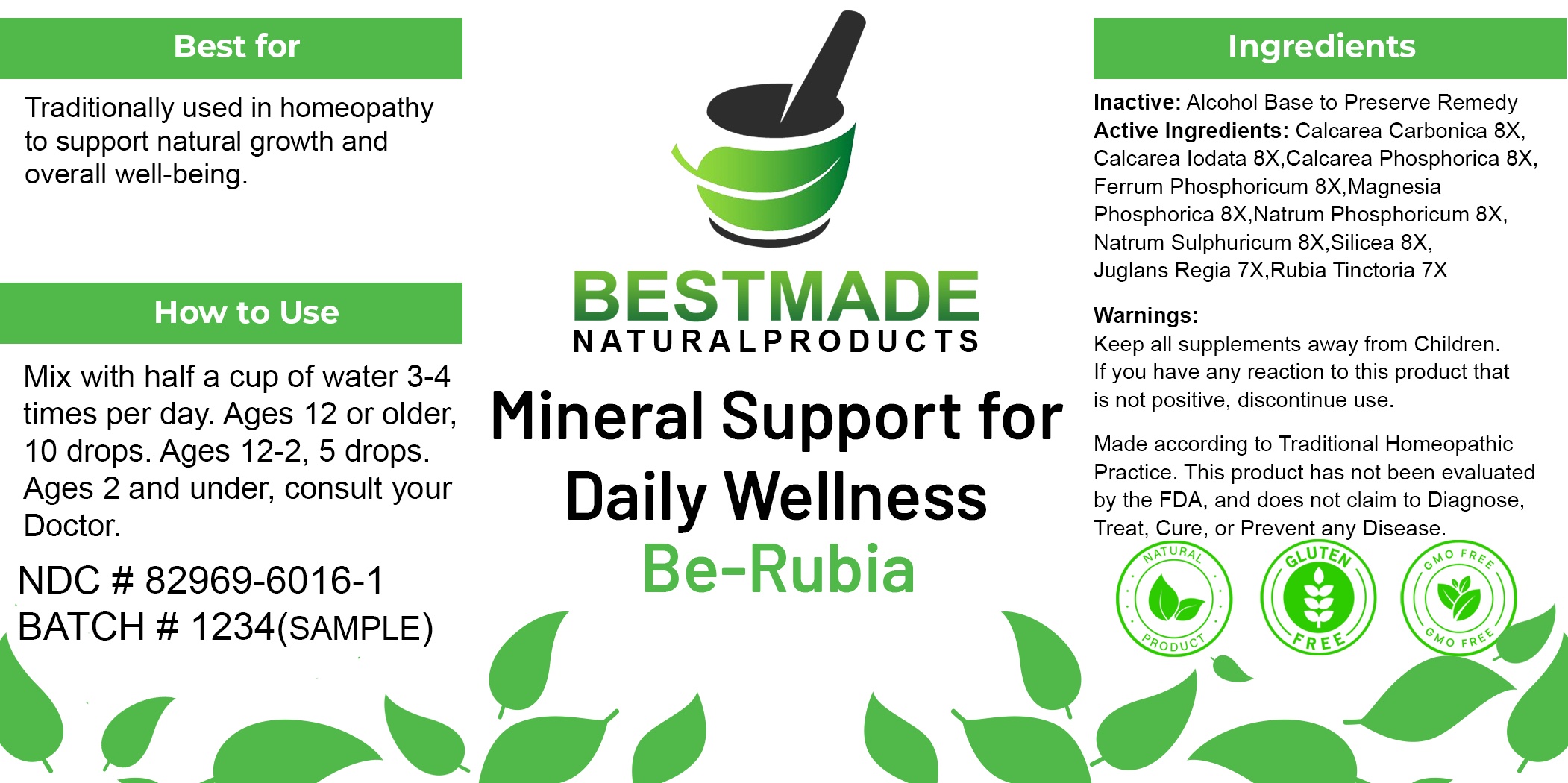 DRUG LABEL: Bestmade Natural Products Daily Wellness - Be-Rubia
NDC: 82969-6016 | Form: LIQUID
Manufacturer: Bestmade Natural Products
Category: homeopathic | Type: HUMAN OTC DRUG LABEL
Date: 20241220

ACTIVE INGREDIENTS: MAGNESIUM PHOSPHATE, DIBASIC TRIHYDRATE 30 [hp_C]/30 [hp_C]; OYSTER SHELL CALCIUM CARBONATE, CRUDE 30 [hp_C]/30 [hp_C]; SODIUM PHOSPHATE, DIBASIC, HEPTAHYDRATE 30 [hp_C]/30 [hp_C]; CALCIUM IODIDE 30 [hp_C]/30 [hp_C]; FERROSOFERRIC PHOSPHATE 30 [hp_C]/30 [hp_C]; TRIBASIC CALCIUM PHOSPHATE 30 [hp_C]/30 [hp_C]; SILICA 30 [hp_C]/30 [hp_C]; SODIUM SULFATE 30 [hp_C]/30 [hp_C]; JUGLANS REGIA FLOWERING TOP 30 [hp_C]/30 [hp_C]; RUBIA TINCTORUM WHOLE 30 [hp_C]/30 [hp_C]
INACTIVE INGREDIENTS: ALCOHOL 30 [hp_C]/30 [hp_C]

Daily Wellness - Be-Rubia

DOSAGE AND ADMINISTRATION

Mix with half a cup of water 3-4
times per day. Ages 12 or older,
10 drops. Ages 12-2, 5 drops.
Ages 2 and under, consult your
Doctor

INDICATIONS AND USAGE

Traditionally used in homeopathy
to support natural growth and
overall well-being.

Inactive: Alcohol Base to Preserve Remedy

Active Ingredients: Calcarea Carbonica 8X
Calcarea lodata 8X,Calcarea Phosphorica 8X
Ferrum Phosphoricum 8X,Magnesia
Phosphorica 8X,Natrum Phosphoricum 8X,
Natrum Sulphuricum 8X, Silicea 8X,
Juglans Regia 7X,Rubia Tinctoria 7X

Keep all supplements away from Children.

PURPOSE

Traditionally used in homeopathy
to support natural growth and
overall well-being.

Warnings:
Keep all supplements away from Children.
If you have any reaction to this product that
is not positive, discontinue use.

Entire package label